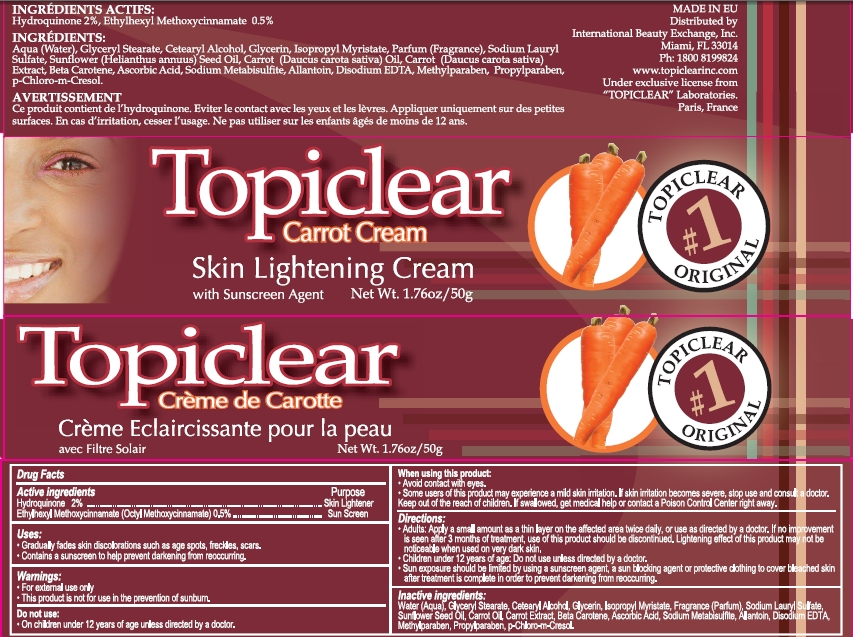 DRUG LABEL: Topiclear Carrot
NDC: 66129-015 | Form: CREAM
Manufacturer: International Beauty Exchange
Category: otc | Type: HUMAN OTC DRUG LABEL
Date: 20110523

ACTIVE INGREDIENTS: HYDROQUINONE 1 g/50 g; OCTINOXATE .25 g/50 g
INACTIVE INGREDIENTS: WATER; GLYCERYL STEARATE CITRATE; CETOSTEARYL ALCOHOL; GLYCERIN; ISOPROPYL MYRISTATE; BETA CAROTENE; ALLANTOIN; ASCORBIC ACID; SODIUM METABISULFITE; CARROT; SODIUM LAURYL SULFATE; EDETATE DISODIUM; METHYLPARABEN; PROPYLPARABEN; CHLOROCRESOL; CARROT SEED OIL; SUNFLOWER OIL

Drug Facts

ACTIVE INGREDIENT

Hydroquinone 2%

Ethylhexyl Methoxycinnamate (Octyl Methoxycinnamate) 0.5%

WARNINGS

For external use only

DO NOT USE

On children under 12 years of age unless directed by a doctor

WHEN USING

Avoid contact with eyes.

PURPOSE

Skin Lightener